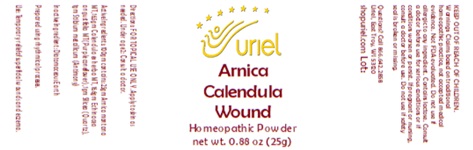 DRUG LABEL: Arnica Calendula Wound
NDC: 48951-1402 | Form: POWDER
Manufacturer: Uriel Pharmacy, Inc
Category: homeopathic | Type: HUMAN OTC DRUG LABEL
Date: 20250630

ACTIVE INGREDIENTS: CALENDULA OFFICINALIS FLOWERING TOP 1 [hp_X]/1 g; ARNICA MONTANA 1 [hp_X]/1 g; ECHINACEA, UNSPECIFIED 1 [hp_X]/1 g; SILICA 1 [hp_X]/1 g; ANTIMONY 1 [hp_X]/1 g
INACTIVE INGREDIENTS: DIATOMACEOUS EARTH

Arnica Calendula Wound

INDICATIONS AND USAGE

Directions: FOR TOPICAL USE ONLY

DOSAGE AND ADMINISTRATION

Apply to skin as needed. Under age 2: Consult a doctor.

ACTIVE INGREDIENT

Active Ingredients: 100gm contains: 25gm Arnica montana MT, 16.5gm Calendula ex herba MT, 16.6gm Echinacea angustifolia MT (Purple coneflower), 1gm Silicea (Quartz), 1gm Stibium metallicum (Antimony)

Inactive Ingredient: Diatomaceous Earth

Prepared using rhythmical processes.

PURPOSE

Use: Temporary relief of superficial wounds and eczema.

KEEP OUT OF REACH OF CHILDREN.

WARNINGS

Warnings: Claims based on traditional homeopathic practice, not accepted medical evidence. Not FDA evaluated. Do not use if allergic to any ingredient. Contains lactose. Consult a doctor before use for serious conditions or if conditions worsen or persist. If pregnant or nursing, consult a doctor before use. Do not use if safety seal is broken or missing.

Questions? Call 866.642.2858
Uriel, East Troy, WI 53120
shopuriel.com Lot: